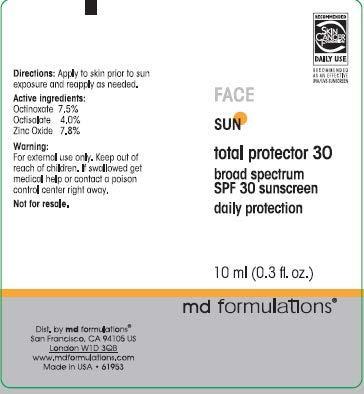 DRUG LABEL: Sun Total Protector 30 broad spectrum SPF 30 daily protection
NDC: 66078-440 | Form: CREAM
Manufacturer: MD Formulation.
Category: otc | Type: HUMAN OTC DRUG LABEL
Date: 20130128

ACTIVE INGREDIENTS: OCTINOXATE 7.5 g/100 g; OCTISALATE 4.0 g/100 g; ZINC OXIDE 7.8 g/100 g
INACTIVE INGREDIENTS: WATER; GLYCERIN; ALLANTOIN; EDETATE DISODIUM; XANTHAN GUM; CETYL HYDROXYETHYLCELLULOSE (350000 MW); METHYLPARABEN; GLYCERYL STEARATE SE; STEARETH-2; GLYCERYL MONOSTEARATE; PEG-100 STEARATE; STEARETH-100; TRICONTANYL POVIDONE (4 TRICONTANYL BRANCHES/REPEAT); C12-15 ALKYL BENZOATE; TOCOPHERYL NICOTINATE, D-.ALPHA.; PROPYLPARABEN; DIMETHICONE; DIAZOLIDINYL UREA; IODOPROPYNYL BUTYLCARBAMATE; PHENOXYETHANOL

Acive ingredients:

Octinoxate 7.5%

Octisalate 4.0%

Zinc Oxide 7.8%

Warning:

For external use only. Keep out of reach of children. If swallowed get medical help or contact a poison control center right away.

Not for resale.

Directions:

Apply to skin prior to sun exposure and reapply as needed.